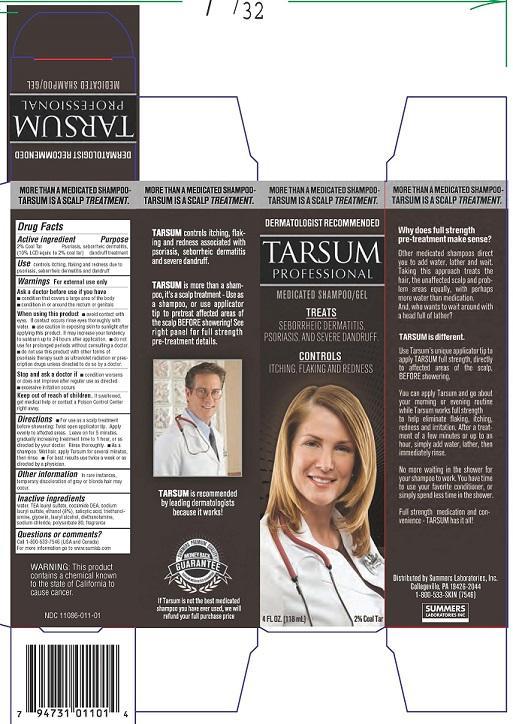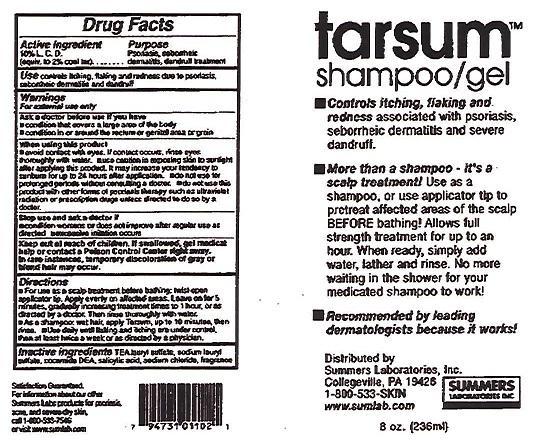 DRUG LABEL: TARSUM PROFESSIONAL
NDC: 11086-011 | Form: SHAMPOO
Manufacturer: Summers Laboratories Inc
Category: otc | Type: HUMAN OTC DRUG LABEL
Date: 20231009

ACTIVE INGREDIENTS: COAL TAR 2 g/100 mL
INACTIVE INGREDIENTS: WATER; TRIETHANOLAMINE LAURYL SULFATE; COCO DIETHANOLAMIDE; SODIUM LAURYL SULFATE; ALCOHOL 8 g/100 mL; SALICYLIC ACID; TROLAMINE; GLYCERIN; LAURYL ALCOHOL; DIETHANOLAMINE; SODIUM CHLORIDE; POLYSORBATE 80

SUMMERS LABS (as PLD) - TARSUM (11086-011)

ACTIVE INGREDIENT

CONTAINS

2% COAL TAR

(10% LCD EQUIV. TO 2% COAL TAR)

PURPOSE

PSORIASIS, SEBORRHEIC DERMATITIS, DANDRUFF TREATMENT

USE

- CONTROLS ITCHING, FLAKING AND REDNESS DUE TO PSORIASIS, SEBORRHEIC DERMATITIS AND DANDRUFF

WARNINGS

FOR EXTERNAL USE ONLY

Ask a doctor before use if you have

- condition that covers a large area of the body
- condition in or around the rectum or genitals

When using this product

- avoid contact with eyes. If contact occurs rinse eyes thoroughly with water.
- use caution in exposing skin to sunlight after applying this product. It may increase your tendency to sunburn up to 24 hours after application.
- do not use for prolonged periods without consulting a doctor.
- do not use this product with other forms of psoriasis therapy such as ultraviolet radiation or prescription drugs unless directed to do so by a doctor.

Stop and ask a doctor if

- condition worsens or does not improve after regular use as directed
- excessive irritation occurs

KEEP OUT OF REACH OF CHILDREN. IF SWALLOWED, GET MEDICAL HELP OR CONTCT A POISON CONTROL CENTER RIGHT AWAY.

Other information

In rare instances, temporary discoloration of gray or blonde hair may occur.

Directions

- For use as a scalp treatment before showering: Twist open applicator tip. Apply evenly to affected areas. Leave on for 5 minutes, gradually increasing treatment time to 1 hour, or as directed by your doctor. Rinse thoroughly.
- As a shampoo: Wet hair, apply Tarsum for several minutes, then rinse.
- For best results use twice a week or as directed by a physician.

Inactive ingredients

water, TEA lauryl sulfate, cocamide DEA, sodium lauryl sulfate, ethanol (8%), salicylic acid, triethanolamine, glycerin, lauryl alcohol, diethanolamine, sodium chloride, polysorbate 80, fragrance

OTHER SAFETY INFORMATION

Store at controlled room temperature

59° to 86° F (15° to 30° C)

Questions or comments?

Call 1-800-533-7546 (USA and Canada)

For more information go to www.sumlab.com